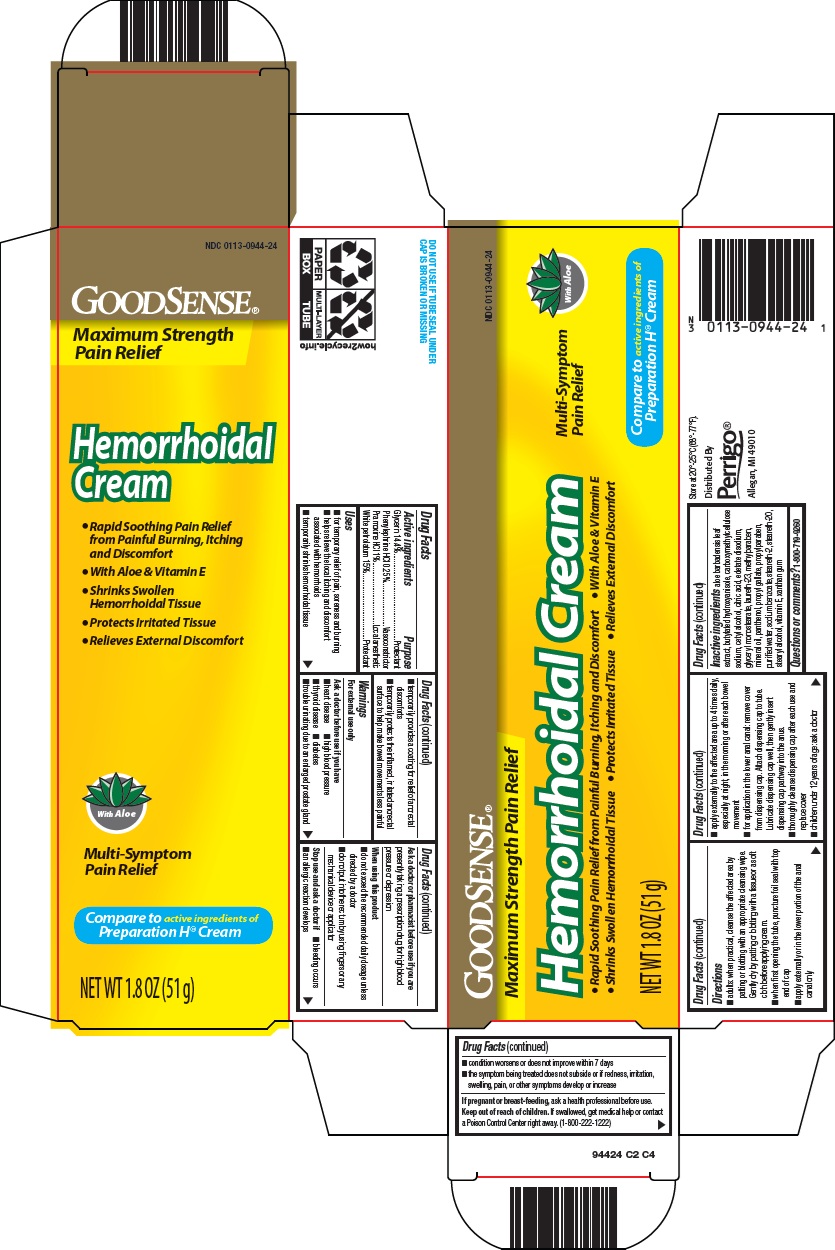 DRUG LABEL: Good Sense Hemorrhoidal
NDC: 0113-0944 | Form: CREAM
Manufacturer: L. Perrigo Company
Category: otc | Type: HUMAN OTC DRUG LABEL
Date: 20260106

ACTIVE INGREDIENTS: GLYCERIN 14.4 g/100 g; PHENYLEPHRINE HYDROCHLORIDE 0.25 g/100 g; PRAMOXINE HYDROCHLORIDE 1 g/100 g; PETROLATUM 15 g/100 g
INACTIVE INGREDIENTS: ALOE VERA LEAF; BUTYLATED HYDROXYANISOLE; CARBOXYMETHYLCELLULOSE SODIUM, UNSPECIFIED; CETYL ALCOHOL; CITRIC ACID MONOHYDRATE; EDETATE DISODIUM; GLYCERYL MONOSTEARATE; LAURETH-23; METHYLPARABEN; MINERAL OIL; PANTHENOL; PROPYL GALLATE; PROPYLPARABEN; WATER; SODIUM BENZOATE; STEARETH-2; STEARETH-20; STEARYL ALCOHOL; .ALPHA.-TOCOPHEROL; XANTHAN GUM

Perrigo Hemorrhoidal Cream Drug Facts

Active ingredients

Glycerin 14.4%

Phenylephrine HCl 0.25%

Pramoxine HCl 1%

White petrolatum 15%

Purpose

Protectant

Vasoconstrictor

Local anesthetic

Uses

- for temporary relief of pain, soreness and burning
- helps relieve the local itching and discomfort associated with hemorrhoids
- temporarily shrinks hemorrhoidal tissue
- temporarily provides a coating for relief of anorectal discomforts
- temporarily protects the inflamed, irritated anorectal surface to help make bowel movements less painful

Warnings

For external use only

Ask a doctor before use if you have

- heart disease
- high blood pressure
- thyroid disease
- diabetes
- trouble urinating due to an enlarged prostate gland

Ask a doctor or pharmacist before use if you are

presently taking a prescription drug for high blood pressure or depression

When using this product

- do not exceed the recommended daily dosage unless directed by a doctor
- do not put into the rectum by using fingers or any mechanical device or applicator

Stop use and ask a doctor if

- bleeding occurs
- an allergic reaction develops
- condition worsens or does not improve within 7 days
- the symptom being treated does not subside or if redness, irritation, swelling, pain, or other symptoms develop or increase

If pregnant or breast-feeding,

ask a health professional before use.

Keep out of reach of children.

If swallowed, get medical help or contact a Poison Control Center right away. (1-800-222-1222)

Directions

- adults: when practical, cleanse the affected area by patting or blotting with an appropriate cleansing wipe. Gently dry by patting or blotting with a tissue or a soft cloth before applying cream.
- when first opening the tube, puncture foil seal with top end of cap
- apply externally or in the lower portion of the anal canal only
- apply externally to the affected area up to 4 times daily, especially at night, in the morning or after each bowel movement
- for application in the lower anal canal: remove cover from dispensing cap. Attach dispensing cap to tube. Lubricate dispensing cap well, then gently insert dispensing cap partway into the anus.
- thoroughly cleanse dispensing cap after each use and replace cover
- children under 12 years of age: ask a doctor

Inactive ingredients

aloe barbadensis leaf extract, butylated hydroxyanisole, carboxymethylcellulose sodium, cetyl alcohol, citric acid, edetate disodium, glyceryl monostearate, laureth-23, methylparaben, mineral oil, panthenol, propyl gallate, propylparaben, purified water, sodium benzoate, steareth-2, steareth-20, stearyl alcohol, vitamin E, xanthan gum

Questions or comments?

1-800-719-9260

Principal Display Panel

GOODSENSE®

Maximum Strength Pain Relief

Hemorrhoidal Cream

Multi-Symptom Pain Relief

with Aloe

• Rapid Soothing Pain Relief from Painful Burning, Itching and Discomfort

• With Aloe & Vitamin E

• Shrinks Swollen Hemorrhoidal Tissue

• Protects Irritated Tissue

• Relieves External Discomfort

Compare to active ingredients of Preparation H® Cream

NET WT 1.8 OZ (51 g)